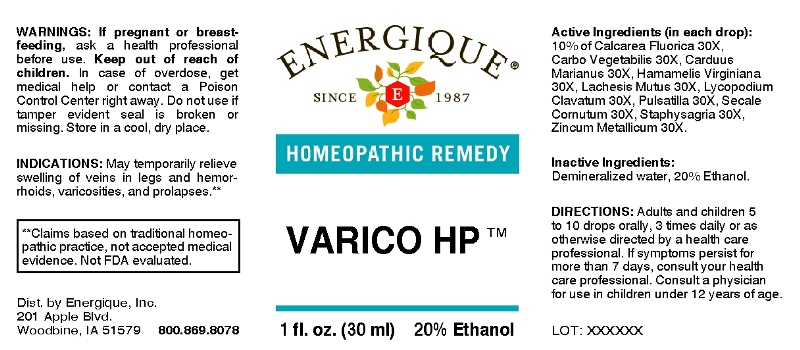 DRUG LABEL: Varico
NDC: 44911-0227 | Form: LIQUID
Manufacturer: Energique, Inc.
Category: homeopathic | Type: HUMAN OTC DRUG LABEL
Date: 20230103

ACTIVE INGREDIENTS: CALCIUM FLUORIDE 30 [hp_X]/1 mL; ACTIVATED CHARCOAL 30 [hp_X]/1 mL; MILK THISTLE 30 [hp_X]/1 mL; HAMAMELIS VIRGINIANA ROOT BARK/STEM BARK 30 [hp_X]/1 mL; LACHESIS MUTA VENOM 30 [hp_X]/1 mL; LYCOPODIUM CLAVATUM SPORE 30 [hp_X]/1 mL; PULSATILLA PRATENSIS WHOLE 30 [hp_X]/1 mL; CLAVICEPS PURPUREA SCLEROTIUM 30 [hp_X]/1 mL; DELPHINIUM STAPHISAGRIA SEED 30 [hp_X]/1 mL; ZINC 30 [hp_X]/1 mL
INACTIVE INGREDIENTS: WATER; ALCOHOL

DRUG FACTS:

ACTIVE INGREDIENTS:

Calcarea Fluorica 30X, Carbo Vegetabilis 30X, Carduus Marianus 30X, Hamamelis Virginiana 30X, Lachesis Mutus 30X, Lycopodium Clavatum 30X, Pulsatilla (Pratensis) 30X, Secale Cornutum 30X, Staphysagria 30X, Zincum Metallicum 30X.

INDICATIONS:

May temporarily relieve swelling of veins and hemorrhoids, varicosities, and prolapses.**

**Claims based on traditional homeopathic practice, not accepted medical evidence. Not FDA evaluated.

WARNINGS:

If pregnant or breast-feeding, ask a health professional before use.

Keep out of reach of children. In case of overdose, get medical help or contact a Poison Control Center right away.

Do not use if tamper evident seal is broken or missing. Store in a cool, dry place.

Keep out of reach of children. In case of overdose, get medical help or contact a Poison Control Center right away.

DIRECTIONS:

Adults and children 5 to 10 drops orally, 3 times daily or as otherwise directed by a health care professional. If symptoms persist, consult your health care professional. Consult a physician for use in children under 12 years of age.

INDICATIONS:

May temporarily relieve swelling of veins and hemorrhoids, varicosities, and prolapses.**

**Claims based on traditional homeopathic practice, not accepted medical evidence. Not FDA evaluated.

INACTIVE INGREDIENTS:

Demineralized water, 20% Ethanol

QUESTIONS:

Dist. by Energique, Inc.

201 Apple Blvd

Woodbine, IA 51579 800-869-8078

PACKAGE LABEL DISPLAY:

ENERGIQUE

SINCE 1987

HOMEOPATHIC REMEDY

VARICO HP

1 fl. oz. (30 ml)